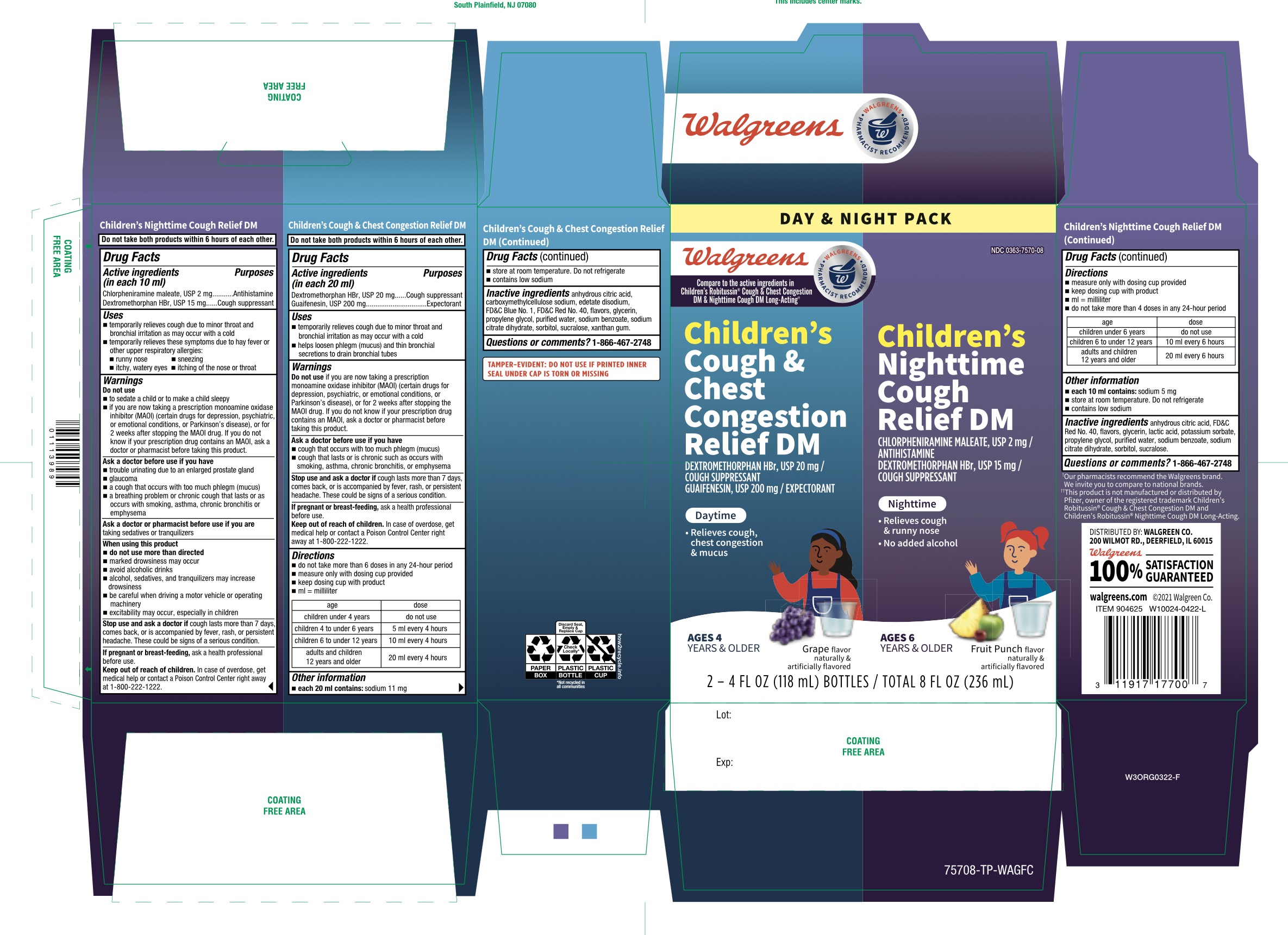 DRUG LABEL: Walgreens DAY and NIGHT PACK
NDC: 0363-7570 | Form: KIT | Route: ORAL
Manufacturer: WALGREEN CO
Category: otc | Type: HUMAN OTC DRUG LABEL
Date: 20251201

ACTIVE INGREDIENTS: DEXTROMETHORPHAN HYDROBROMIDE 20 mg/20 mL; GUAIFENESIN 200 mg/20 mL; CHLORPHENIRAMINE MALEATE 2 mg/10 mL; DEXTROMETHORPHAN HYDROBROMIDE 15 mg/10 mL
INACTIVE INGREDIENTS: ANHYDROUS CITRIC ACID; CARBOXYMETHYLCELLULOSE SODIUM, UNSPECIFIED; EDETATE DISODIUM; FD&C BLUE NO. 1; FD&C RED NO. 40; GLYCERIN; PROPYLENE GLYCOL; WATER; SODIUM BENZOATE; SODIUM CITRATE, UNSPECIFIED FORM; SORBITOL; SUCRALOSE; XANTHAN GUM; ANHYDROUS CITRIC ACID; FD&C RED NO. 40; GLYCERIN; LACTIC ACID, UNSPECIFIED FORM; POTASSIUM SORBATE; PROPYLENE GLYCOL; WATER; SODIUM BENZOATE; SODIUM CITRATE, UNSPECIFIED FORM; SORBITOL; SUCRALOSE

Walgreen Children’s Daytime & Night-Time Cough and Chest Congestion DM

Active ingredients Day Time (in each 20 mL)

Dextromethorphan HBr USP 20 mg

Guaifenesin. USP 200 mg

Active ingredients for Nighttime (in each 10 mL)

Chlorpheniramine maleate, USP 2 mg

Dextromethorphan HBr USP 15 mg

Purposes for Daytime Wal-Tussin®DM

Cough suppressant

Expectorant

Purpose for Nighttime Wal-Tussin®DM

Antihistamine

Cough suppressant

Uses

DAYTIME

- temporarily relieves cough due to minor throat and bronchial irritation as may occur with a cold
- helps loosen phlegm (mucus) and thin bronchial secretions to drain bronchial tubes

NIGHTTIME

- temporarily relieves cough due to minor throat and bronchial irritation as may occur with a cold
- temporarily relieves these symptoms due to hay fever or other upper respiratory allergies:
  - runny nose
  - sneezing
  - itching of the nose or throat
  - itchy, watery eyes

Warnings

Do not us

DAYTIME

- If you are now taking a prescription monoamine oxidase inhibitor (MAOI) (certain drugs for depression, psychiatric or emotional conditions, or Parkinson's disease), or for 2 weeks after stopping the MAOI drug. If you do not know if your prescription drug contains an MAOI, ask a doctor or pharmacist before taking this product.

NIGHTTIME

- to sedate a child or to make a child sleepy
- if you are now taking a prescription monoamine oxidase inhibitor (MAOI) (certain drugs for depression, psychiatric or emotional conditions, or Parkinson's disease), or for 2 weeks after stopping the MAOI drug. If you do not know if your prescription drug contains an MAOI, ask a doctor or pharmacist before taking this product.

Ask a doctor before use if you have

DAYTIME

- cough that occurs with too much phlegm (mucus)
- cough that lasts or is chronic such as occurs with smoking, asthma, chronic bronchitis or emphysema

NIGHTTIME

- trouble urinating due to an enlarges prostate gland
- glaucoma
- a cough that occurs with too much phlegm (mucus)
- a breathing problem or chronic cough that lasts or as occurs with smoking, asthma, chronic bronchitis or emphysema

Ask a doctor or pharmacist before use if you are

NIGHTTIME

taking sedatives or tranquilizers.

When using this product

NIGHTTIME

- do not use more than directed.
- marked drowsiness may occur
- avoid alcoholic drinks
- alcohol, sedatives and tranquilizers may increase drowsiness
- be careful when driving a motor vehicle or operating machinery
- excitability may occur, especially in children

Stop use and ask a doctor if

DAYTIME

- cough last more than 7 days, comes back or is accompanied by fever, rash, or persistent headache. These could be signs of a serious condition.

NIGHTTIME

- cough last more than 7 days, comes back or is accompanied by fever, rash, or persistent headache. These could be signs of a serious condition.

If pregnant or breast-feeding,

DAYTIME

ask a health professional before use.

NIGHTTIME

ask a health professional before use

Keep out of reach of children.

DAYTIME

In case of overdose, get medical help or contact a Poison Control Center (1-800-222-1222) right away.

NIGHTTIME

In case of overdose, get medical help or contact a Poison Control Center (1-800-222-1222) right away

Directions

Daytime Wal-Tussin®DM

- do not take more than 6 doses in any 24-hour period
- measure only with dosing cup provided.
- keep dosing cup with product
- mL= milliliter

age | dose
Children under 4 years | Do not use
Children 4 to under 6 years | 5 mL every 4 hours
Children 6 to under 12 years | 10 mL every 4 hours
Adults and children 12 years and older | 20 mL every 4 hours

Nighttime Wal-Tussin®DM

- do not take more than 4 doses in any 24-hour period
- measure only with dosing cup provided.
- keep dosing cup with product
- mL= milliliter

age | dose
Children under 6 years | Do not use
Children 6 to under 12 years | 10 mL every 6 hours
Adults and children 12 years and older | 20 mL every 6 hours

Other information

DAYTIME Wal-Tussin DM

- each 20 mL contains:sodium 11 mg
- store at room temperature. Do not refrigerate
- contain low sodium
- do not use if printed seal under cap is torn or missing

Nighttime Wal-Tussin DM

- each 10 mL contains:sodium 6 mg
- store at room temperature. Do not refrigerate
- contain low sodium
- do not use if printed seal under cap is torn or missing

Inactive ingredients

Inactive ingredients for Day TimeWal-Tussin DM

anhydrous citric acid, carboxymethylcellulose sodium, edetate disodium, FD &C Blue No. 1, FD&C Red No. 40, natural and artificial flavors, glycerin, propylene glycol, purified water, sodium benzoate, sodium citrate, sorbitol, sucralose, xanthan gum

Inactive ingredients for Night TimeWal-Tussin DM

anhydrous citric acid, FD&C Red No. 40, natural and artificial flavors, glycerin, lactic acid, potassium sorbate, propylene glycol, purified water, sodium benzoate, sodium citrate, sorbitol, sucralose

Questions or comments?

1-866-467-2748

Principal Display Panel

Compare to Children's Robitussin®Cough & Chest Congestion DM* & Nighttime Cough DM Long-Active active ingredients††

Children's

Cough & Chest Congestions DM

Wal-Tussin®DM

DEXTROMETHORPHAN HBr, USP 20 mg/ 20 mL

COUGH SUPPRESSANT

GUAIFENESIN, USP 200 mg

EXPECTORANT

DAYTIME

NON-DROWSY

Relieves cough, chest congestion & mucus

4 YEARS & OVER

GRAPE FLAVOR

Naturally and Artificially Flavored

Dosage cup included

2 - 4 FL OZ (118 mL) BOTTLES / TOTAL – 8 FL OZ (236 mL)

††This product is not manufactured or distributed by Pfizer, the distributor of Children’s Robitussin®Cough & Chest Congestion DM.

Children's

Nighttime Cough DM

Wal-Tussin®DM

CHLORPHENIRAMINE MALEATE, USP 2 mg / 10 mL

ANTIHISTAMINE

DEXTROMETHORPHAN HBr, USP 15 mg / 10 mL

COUGH SUPPRESSANT

NIGHTTIME

- Relieves cough & runny nose

Alcohol free

6 YEARS & OLDER

Fruit Punch Flavor

Naturally and Artificially Flavored

Dosage cup included

2 - 4 FL OZ (118 mL) BOTTLES TOTAL – 8 FL OZ (236 mL)

††This product is not manufactured or distributed by Pfizer, the distributor of Children’s Robitussin®Nighttime Cough DM Long-Acting.

Walgreens

PHARMACIST RECOMMENDED

TAMPER EVIDENT: DO NOT USE IF PRINTED INNER SEAL UNDER CAP IS BROKEN OR MISSING

DISTRIBUTED BY: WALGREENS CO.

200 WILMOT RD. DEERFIELD, IL 60015

Walgreens 10% SATISFACTION GUARANTEED

walgreens.com ©2020 Walgreen Co.